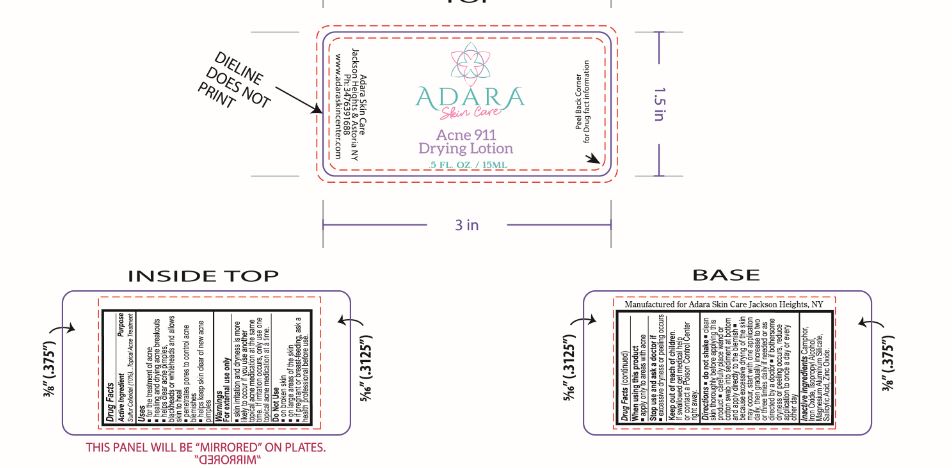 DRUG LABEL: ADARA Acne 911 Drying
NDC: 76348-890 | Form: SUSPENSION
Manufacturer: Renu Laboratories, Inc.
Category: otc | Type: HUMAN OTC DRUG LABEL
Date: 20230814

ACTIVE INGREDIENTS: SULFUR 1.4 g/14 g
INACTIVE INGREDIENTS: MAGNESIUM ALUMINUM SILICATE; ZINC OXIDE; SALICYLIC ACID; CAMPHOR (SYNTHETIC); ISOPROPYL ALCOHOL; FERRIC OXIDE RED

Drying Lotion

Active Ingredient

Sulfur Colloidal (10%)

Purpose

Topical Acne Treatment

Uses

- for the treatment of acne
- healing and drying acne breakouts
- helps clear acne pimples, blackheads or whiteheads and allows skin to heal
- penetrates pores to control acne blemishes
- helps keep skin clear of new acne pimples

Warnings

For external use only

- skin irritation and dryness is more likely to occur if you use another topical acne medication at the same time.
  If irritation occurs, only use one topical acne medication at a time.

Do Not Use

- on broken skin
- on large areas of the skin
- if pregnant or breast-feeding, ask a health professional before use.

When using this product

- apply only to areas with acne

Stop use and ask a doctor if

- excessive dryness or peeling occurs

Keep out of reach of children.

If swallowed get medical help or contact a Poison Control Center right away.

Directions

Do Not Shake

- clean skin thoroughly before applying this product
- carefully place wand or cotton swab into sediment at bottom and apply directly to the blemish
- because excessive drying of the skin may occur, start with one application daily, then gradually increase to two or three times daily if needed or as directed
  by a doctor
- if bothersome dryness or peeling occurs, reduce application to once a day or every other day

Inactive ingredients

Camphor, Iron Oxide, Isopropyl Alcohol, Magnesium Aluminum Silicate, Salicylic Acid,
Zinc Oxide.

BOTTLE LABEL ART SHOWN BELOW